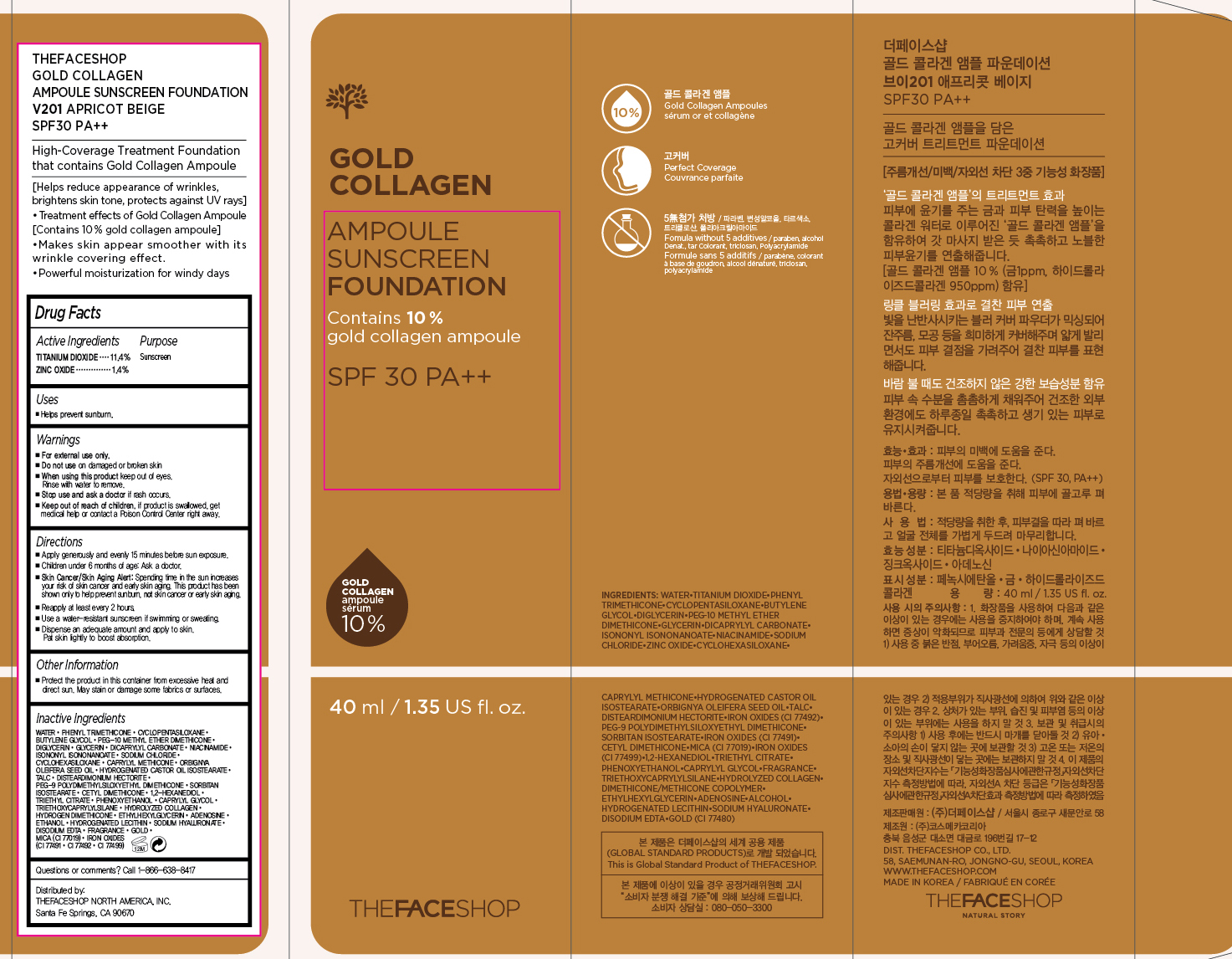 DRUG LABEL: GOLD COLLAGEN
NDC: 51523-257 | Form: CREAM
Manufacturer: THEFACESHOP CO., LTD.
Category: otc | Type: HUMAN OTC DRUG LABEL
Date: 20160101

ACTIVE INGREDIENTS: TITANIUM DIOXIDE 4.6 g/40 mL; ZINC OXIDE 0.6 g/40 mL
INACTIVE INGREDIENTS: WATER

GOLD COLLAGEN AMPOULE SUNSCREEN FOUNDATION SPF 30 V201 APRICOT BEIGE 34200257

Active Ingredients

Titanium Dioxide 11.4%

Zinc Oxide 1.4%

Purpose

Sunscreen

Sunscreen

Uses

Helps prevent sunburn

Warnings

For external use only.

Do not use on damaged or broken skin

When using this product keep out of eyes. Rinse with water to remove.

Stop use and ask a doctor if rash occurs.

Keep out of reach of children.

If product is swallowed, get medical help or contact a Poison Control Center right away.

Directions

Apply generously and evenly 15 minutes before sun exposure.
Children under 6 months of age: Ask a doctor.
Skin Cancer/Skin Aging Alert: Spending time in the sun increases your risk of skin cancer and early skin aging. This product has been shown only to help prevent sunburn, not skin cancer or early skin aging.
Reapply at least every 2 hours.
Use a water-resistant sunscreen if swimming or sweating.

Dispense an adequate amount and apply to skin.

Pat skin lightly to boost absorption.

Other Information

Protect the product in this container from excessive heat and direct sun.

May stain or damage some fabrics or surfaces.

Inactive Ingredients

Water, Phenyl Trimethicone, Cyclopentasiloxane, Butylene Glycol, PEG-10 Methyl Ether Dimethicone, Diglycerin, Glycerin, Dicaprylyl Carbonate, Niacinamide, Isononyl Isononanoate, Sodium Chloride, Cyclohexasiloxane, Caprylyl Methicone, Orbignya Oleifera Seed Oil, Hydrogenated Castor Oil Isostearate, Talc, Disteardimonium Hectorite, PEG-9 Polydimethylsiloxyethyl Dimethicone, Sorbitan Isostearate, Cetyl Dimethicone, 1,2-Hexanediol, Triethyl Citrate, Phenoxyethanol, Caprylyl Glycol, Triethoxycaprylylsilane, Hydrolyzed Collagen, Hydrogen Dimethicone, Ethylhexylglycerin, Adenosine, Ethanol, Hydrogenated Lecithin, Sodium Hyaluronate, Disodium EDTA, Fragrance, Gold, Mica (CI 77019), Iron Oxides (CI 77491, CI 77492, CI 77499)

Questions or comments? Call 1-866-638-8417

Distributed by:

THEFACESHOP NORTH AMERICA, INC.

Santa Fe Springs, CA 90670

PACKAGE LABEL

THEFACESHOP

GOLD COLLAGEN

AMPOULE SUNSCREEN FOUNDATION

V201 APRICOT BEIGE

SPF30 PA++